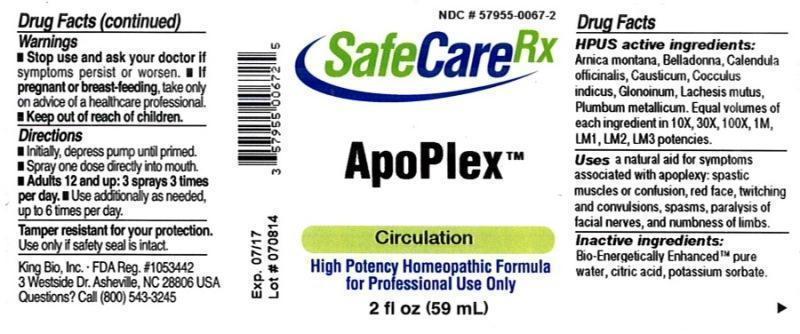 DRUG LABEL: ApoPlex
NDC: 57955-0067 | Form: LIQUID
Manufacturer: King Bio Inc.
Category: homeopathic | Type: HUMAN OTC DRUG LABEL
Date: 20150306

ACTIVE INGREDIENTS: ARNICA MONTANA 10 [hp_X]/59 mL; ATROPA BELLADONNA 10 [hp_X]/59 mL; CALENDULA OFFICINALIS FLOWERING TOP 10 [hp_X]/59 mL; CAUSTICUM 10 [hp_X]/59 mL; ANAMIRTA COCCULUS SEED 10 [hp_X]/59 mL; NITROGLYCERIN 10 [hp_X]/59 mL; LACHESIS MUTA VENOM 10 [hp_X]/59 mL; LEAD 10 [hp_X]/59 mL
INACTIVE INGREDIENTS: WATER; ANHYDROUS CITRIC ACID; POTASSIUM SORBATE

ApoPlex

ACTIVE INGREDIENT

Drug Facts__________________________________________________________________________________________________________

HPUS active ingredients: Arnica montana, Belladonna, Calendula officinalis, Causticum, Cocculus indicus, Glonoinum, Lachesis mutus, Plumbum metallicum. Equal volumes of each ingredient in 10X, 30X, 100X, 1M, LM1, LM2, LM3 potencies.

INDICATIONS AND USAGE

Uses a natural aid for symptoms associated with apoplexy: spastic muscles or confusion, red face, twitching and convulsions, spasms, paralysis of facial nerves, and numbness of limbs.

Inactive Ingredients:

Bio-Energetically Enhanced™ pure water, citric acid and potassium sorbate.

Warnings

- Stop use and ask your doctor if symptoms persist or worsen.
- If pregnant or breast-feeding, take only on advice of a healthcare professional.

- Keep out of reach of children.

Directions

- Initially, depress pump until primed.
- Spray one dose directly into mouth.
- Adults 12 and up: 3 sprays 3 times per day
- Use additionally as needed, up to 6 times per day.

OTHER SAFETY INFORMATION

Tamper resistant for your protection. Use only if safety seal is intact.

PURPOSE

Uses a natural aid for symptoms associated with apoplexy:

- spastic muscles or confusion
- red face
- twitching and convulsions
- spasms
- paralysis of facial nerves, and numbness of limbs